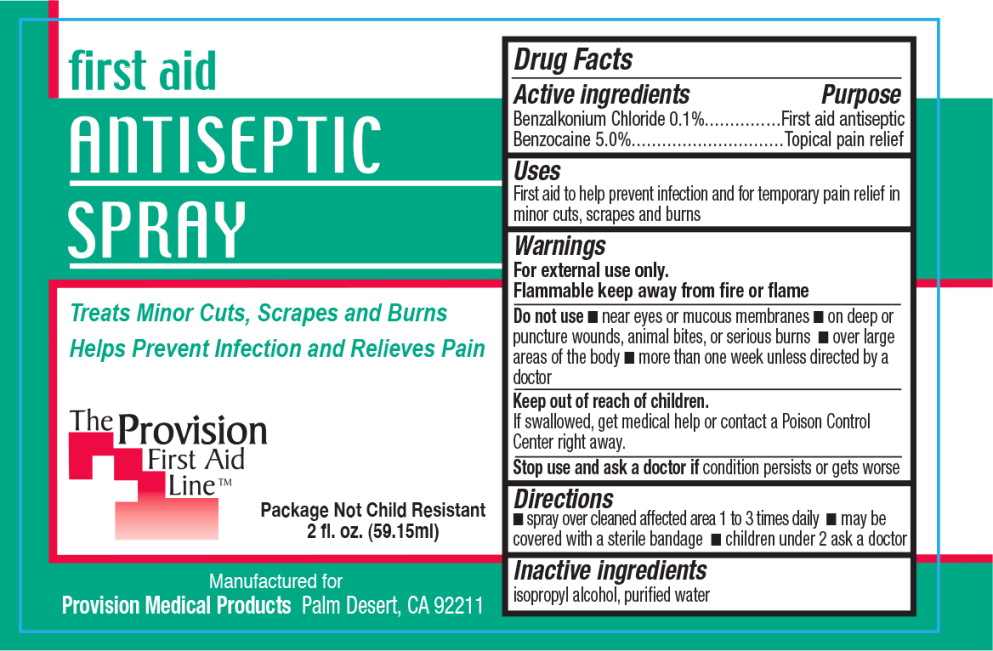 DRUG LABEL: First Aid Antiseptic
NDC: 69103-3501 | Form: SPRAY
Manufacturer: Provision Medical
Category: otc | Type: HUMAN OTC DRUG LABEL
Date: 20140829

ACTIVE INGREDIENTS: benzalkonium chloride 1 g/1 L; benzocaine 50 g/1 L
INACTIVE INGREDIENTS: isopropyl alcohol; water

Drug Facts

Active ingredients

Benzaikonium Chloride 0.1%

Benzocaine 5.0%

Purpose

First aid antiseptic

Topical pain relief

Uses

First aid to help prevent infection and for temporary pain relief in minor cuts, scrapes and burns

Warnings

For external use only.

Flammable keep away from fire or flame

Do not use

- near eyes or mucous membranes
- on deep or puncture wounds, animal bites, or serious burns
- over large areas of the body
- more than one week unless directed by a doctor

Keep out of reach of children.

If swallowed, get medical help or contact a Poison Control Center right away.

Stop use and ask a doctor if condition persists or gets worse

Directions

- spray over cleaned affected area 1 to 3 times daily
- may be covered with a sterile bandage
- children under 2 ask a doctor

Inactive ingredients

isopropyl alcohol, purified water

Principal Display Panel - Bottle Label

first aid
ANTISEPTIC
SPRAY

Treats Minor Cuts, Scrapes and Burns
Helps Prevent Infection and Relieves Pain

Package Not Child Resistant

2 fl. oz. (59.15ml)

Manufactured for

Provision Medical Products Palm Desert, CA 92211